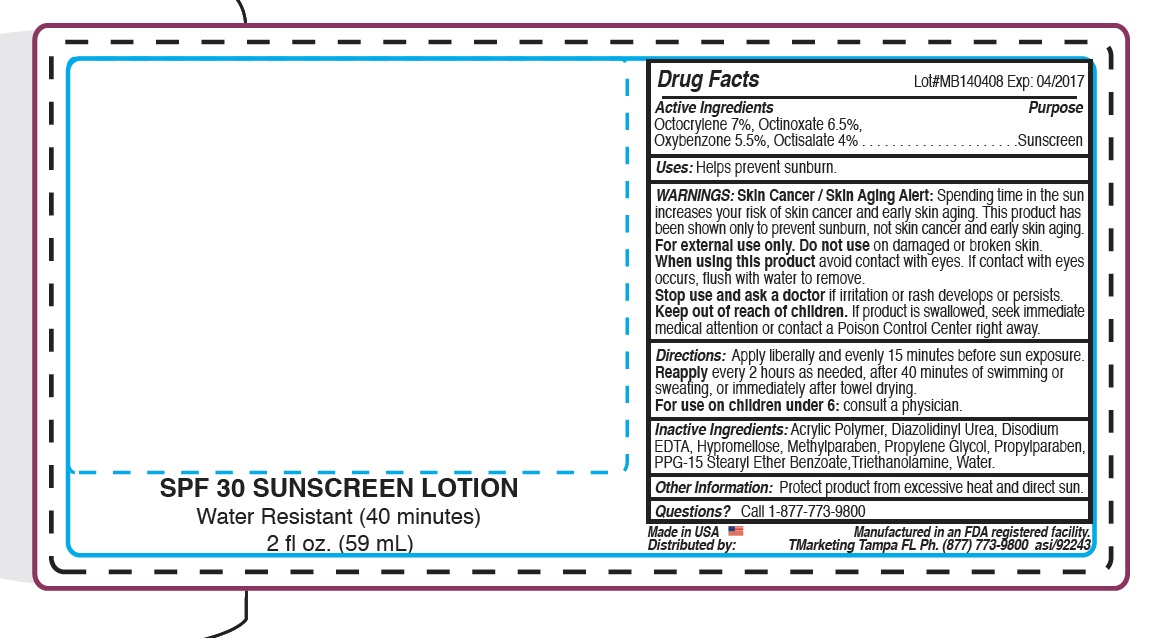 DRUG LABEL: Skin Crave spf30 sunscreen
NDC: 58418-223 | Form: LOTION
Manufacturer: Tropical Enterprises International, Inc.
Category: otc | Type: HUMAN OTC DRUG LABEL
Date: 20141201

ACTIVE INGREDIENTS: Octisalate 4 mg/1 mL; Oxybenzone 5.5 mg/1 mL; Octocrylene 7 mg/1 mL; Octinoxate 6.5 mg/1 mL
INACTIVE INGREDIENTS: METHYLPARABEN; PROPYLPARABEN; WATER; MAGNESIUM DISODIUM EDTA; HYPROMELLOSE 2208 (100 MPA.S); DIAZOLIDINYL UREA; PPG-15 STEARYL ETHER BENZOATE; CUPRIC TRIETHANOLAMINE

Spf30 Sunscreen lotion (non broad spectrum)

DOSAGE AND ADMINISTRATION

Directions: Apply liberally and evenly 15 minutes before sun exposure.

Reapply every 2 hours as needed, after 40 minutes of swimming or sweating, or immedaitely after towel dry9ing.

For use on children under 6 months: consult a physician

INACTIVE INGREDIENT

Inactive Ingredients: Acrylic Polymer, Diazolidinyl Urea, Disodium EDTA, Hypromellose, Methylparaben, Propylene Glycol, Propylparaben, PPG-15 Stearyl Ether Benzoate, Triethanolamine, Water

INDICATIONS AND USAGE

Uses: Helps prevent sunburn.

Keep out of reach of children. If product is swallowed, seek immediate medical attention or contact a Poison Control Center right away.

Purpose:

Sunscreen

Active Ingredients:

Octocrylene 7%, Octinoxate 6.5%

Oxybenone 5.5 %, Octisalate 4%

WARNINGS

WARNINGS: Skin Cancer/ Sking Aging Alert: Spending time in the sun

increases your risk of skin cancer and early skin aging. This product has been shown only to prevent sunburn, not skin cancer and early skin aging.

For external use only. Do not use on damaged or broken skin.

When using this product avoid contact with eyes. If contact with eyes occurs, flush with water to remove.

Stop use and ask a doctor if irritation or rash develops or persists.

Keep out of reach of children. If product is swallowed, seek immediate medical attention or contact a Poison Control Center right away.